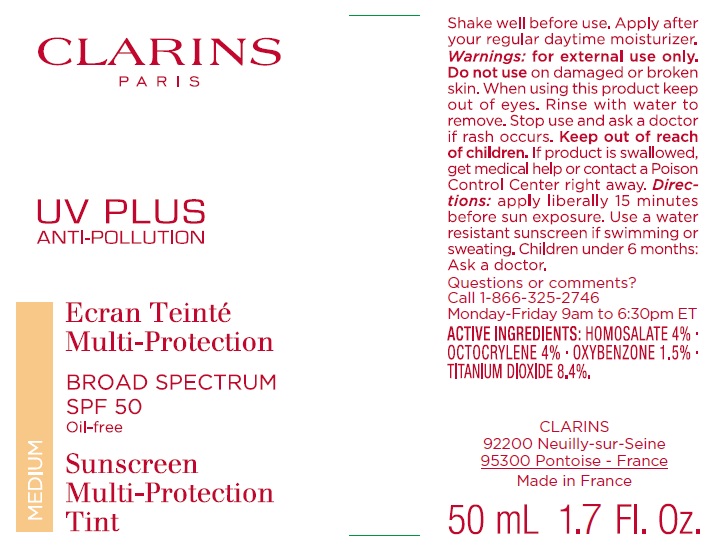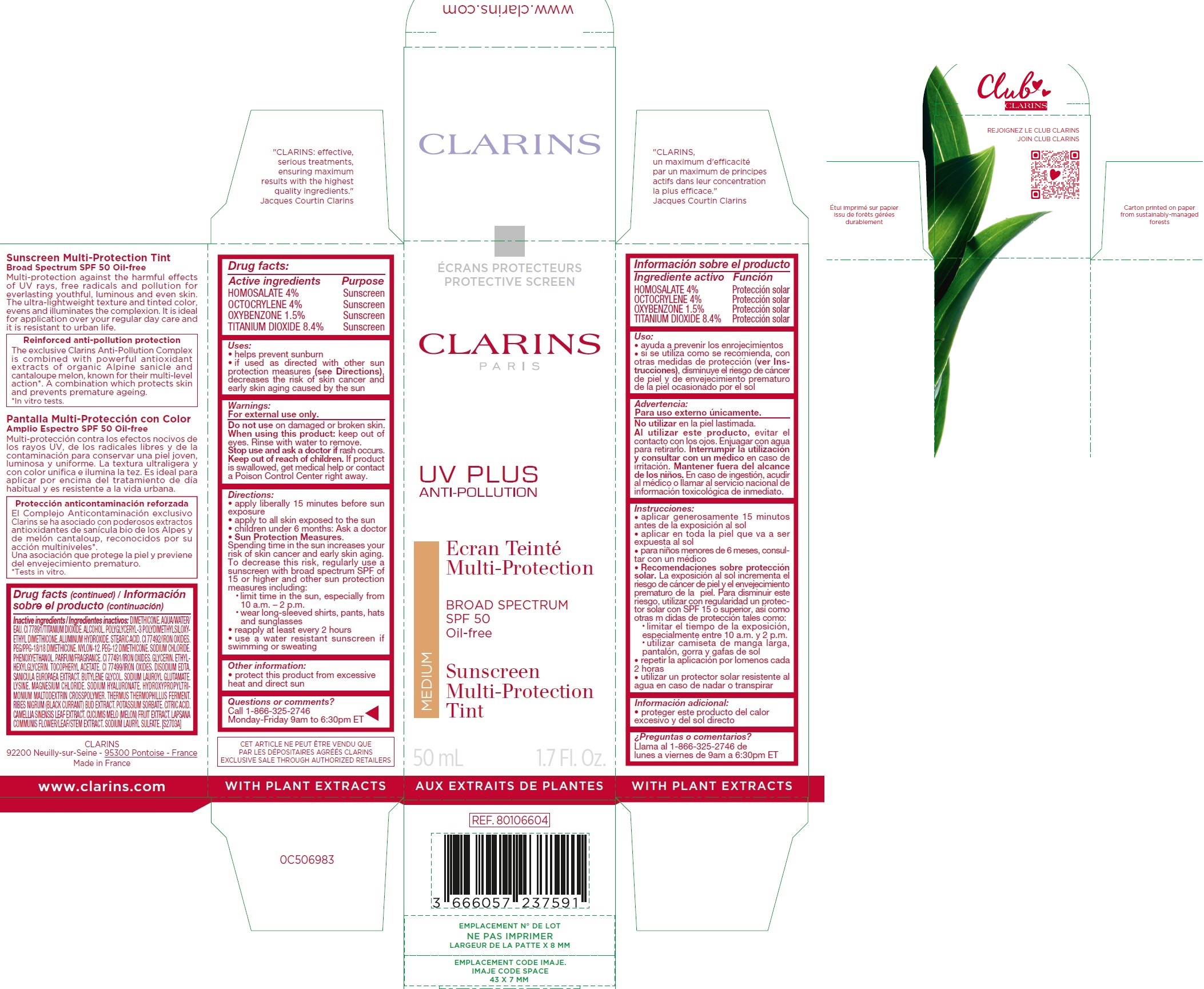 DRUG LABEL: Clarins UV PLUS ANTI-POLLUTION B.S. SPF 50, Sunscreen Multi-Protection Tint Medium
NDC: 58668-1619 | Form: LIQUID
Manufacturer: Laboratoires Clarins
Category: otc | Type: HUMAN OTC DRUG LABEL
Date: 20240220

ACTIVE INGREDIENTS: HOMOSALATE 40 mg/1 mL; OCTOCRYLENE 40 mg/1 mL; OXYBENZONE 15 mg/1 mL; TITANIUM DIOXIDE 84 mg/1 mL
INACTIVE INGREDIENTS: DIMETHICONE; WATER; ALCOHOL; ALUMINUM HYDROXIDE; STEARIC ACID; FERRIC OXIDE YELLOW; PEG/PPG-18/18 DIMETHICONE; NYLON-12; PEG-12 DIMETHICONE; SODIUM CHLORIDE; PHENOXYETHANOL; FERRIC OXIDE RED; GLYCERIN; ETHYLHEXYLGLYCERIN; .ALPHA.-TOCOPHEROL ACETATE; FERROSOFERRIC OXIDE; EDETATE DISODIUM; BUTYLENE GLYCOL; SODIUM LAUROYL GLUTAMATE; LYSINE; MAGNESIUM CHLORIDE; HYALURONATE SODIUM; RIBES NIGRUM FLOWER BUD; POTASSIUM SORBATE; CITRIC ACID MONOHYDRATE; GREEN TEA LEAF; MUSKMELON; LAPSANA COMMUNIS FLOWERING TOP; SODIUM LAURYL SULFATE

CLARINS UV PLUS ANTI-POLLUTION SUNSCREEN MULTI-PROTECTION BROAD SPECTRUM SPF 50 OIL-FREE - MEDIUM

Active ingredients

HOMOSALATE 4%

OCTOCRYLENE 4%

OXYBENZONE 1.5%

TITANIUM DIOXIDE 8.4%

Purpose

Sunscreen

Uses:

• helps prevent sunburn
• if used as directed with other sun protection measures (see Directions), decreases the risk of skin cancer and early skin aging caused by the sun

Warnings:

For external use only.

Do not use

on damaged or broken skin.

When using this product:

keep out of eyes. Rinse with water to remove.

Stop use and ask a doctor if

rash occurs.

Keep out of reach of children.

If product is swallowed, get medical help or contact a Poison Control Center right away.

Directions:

• apply liberally 15 minutes before sun exposure
• apply to all skin exposed to the sun
• children under 6 months: Ask a doctor
• Sun Protection Measures. Spending time in the sun increases your risk of skin cancer and early skin aging. To decrease this risk, regularly use a sunscreen with broad spectrum SPF of 15 or higher and other sun protection measures including:
• limit time in the sun, especially from 10 a.m. – 2 p.m.
• wear long-sleeved shirts, pants, hats and sunglasses
• reapply at least every 2 hours
• use a water resistant sunscreen if swimming or sweating

Other information:

• protect this product from excessive heat and direct sun

Questions or comments?

Call 1-866-325-2746 Monday-Friday 9am to 6:30pm ET

Inactive ingredients:

DIMETHICONE. AQUA/WATER/. CI 77891/TITANIUM DIOXIDE. ALCOHOL. POLYGLYCERYL-3 POLYDIMETHYLSILOXYETHYL DIMETHICONE. ALUMINUM HYDROXIDE. STEARIC ACID. CI 77492/IRON OXIDES. PEG/PPG-18/18 DIMETHICONE. NYLON-12. PEG-12 DIMETHICONE. SODIUM CHLORIDE. PHENOXYETHANOL. PARFUM/FRAGRANCE. CI 77491/IRON OXIDES. GLYCERIN. ETHYLHEXYLGLYCERIN. TOCOPHERYL ACETATE. CI 77499/IRON OXIDES. DISODIUM EDTA. SANICULA EUROPAEA EXTRACT. BUTYLENE GLYCOL. SODIUM LAUROYL GLUTAMATE. LYSINE. MAGNESIUM CHLORIDE. SODIUM HYALURONATE. HYDROXYPROPYLTRIMONIUM MALTODEXTRIN CROSSPOLYMER. THERMUS THERMOPHILLUS FERMENT. RIBES NIGRUM (BLACK CURRANT) BUD EXTRACT. POTASSIUM SORBATE. CITRIC ACID. CAMELLIA SINENSIS LEAF EXTRACT. CUCUMIS MELO (MELON) FRUIT EXTRACT. LAPSANA COMMUNIS FLOWER/LEAF/STEM EXTRACT. SODIUM LAURYL SULFATE. [S2703A]